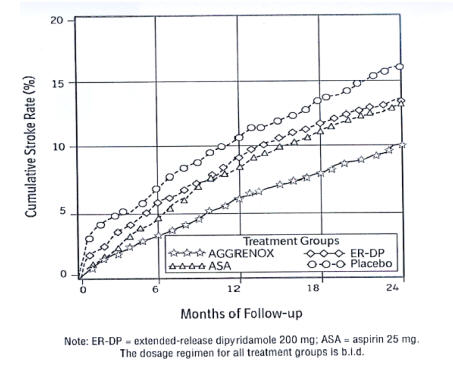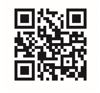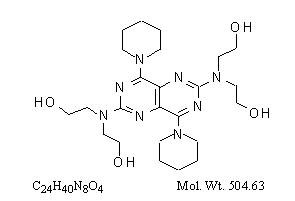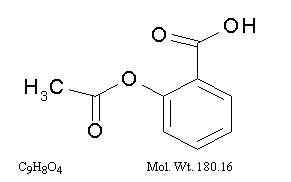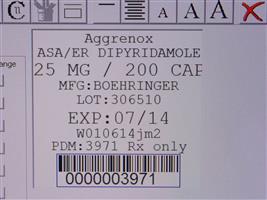 DRUG LABEL: Aggrenox
NDC: 68151-3971 | Form: CAPSULE, EXTENDED RELEASE
Manufacturer: Carilion Materials Management
Category: prescription | Type: HUMAN PRESCRIPTION DRUG LABEL
Date: 20160806

ACTIVE INGREDIENTS: ASPIRIN 25 mg/1 1; DIPYRIDAMOLE 200 mg/1 1

HIGHLIGHTS OF PRESCRIBING INFORMATION

These highlights do not include all the information needed to use AGGRENOX safely and effectively. See full prescribing information for AGGRENOX.
AGGRENOX® (aspirin/extended-release dipyridamole) Capsules
Initial U.S. Approval: 1999

1 INDICATIONS AND USAGE

- AGGRENOX is a combination antiplatelet agent indicated to reduce the risk of stroke in patients who have had transient ischemia of the brain or completed ischemic stroke due to thrombosis (1)

2 DOSAGE AND ADMINISTRATION

- One capsule twice daily (morning and evening) with or without food (2)
- In case of intolerable headaches during initial treatment, switch to one capsule at bedtime and low-dose aspirin in the morning; resume BID dosing within one week (2)
- Do not chew capsule (2)
- Not interchangeable with the individual components of aspirin and dipyridamole tablets (2)
- Dispense in this unit-of-use container (16)

3 DOSAGE FORMS AND STRENGTHS

- Capsule: 25 mg aspirin/200 mg extended-release dipyridamole (3)

4 CONTRAINDICATIONS

- Hypersensitivity to any product ingredients (4.1)
- Patients with known allergy to NSAIDs (4.2)
- Patients with the syndrome of asthma, rhinitis, and nasal polyps (4.2)

5 WARNINGS AND PRECAUTIONS

- AGGRENOX increases the risk of bleeding (5.1)
- Avoid use in patients with severe hepatic or renal insufficiency (5.2, 5.3)
- Can cause fetal harm when administered to a pregnant woman, especially in the third trimester (5.4)

6 ADVERSE REACTIONS

- The most frequently reported adverse reactions (>10% and greater than placebo) were headache, dyspepsia, abdominal pain, nausea, and diarrhea (6)

To report SUSPECTED ADVERSE REACTIONS, contact Boehringer Ingelheim Pharmaceuticals, Inc. at (800) 542-6257 or (800) 459-9906 TTY or FDA at 1-800-FDA-1088 or www.fda.gov/medwatch.

7 DRUG INTERACTIONS

- Co-administration with anticoagulants, antiplatelets, or NSAIDs can increase risk of bleeding (7.1)
- Decreased renal function can occur with co-administration with NSAIDs (7.1)

8 USE IN SPECIFIC POPULATIONS

- Pregnancy Category D (8.1)

FULL PRESCRIBING INFORMATION

1 INDICATIONS AND USAGE

AGGRENOX is indicated to reduce the risk of stroke in patients who have had transient ischemia of the brain or completed ischemic stroke due to thrombosis.

2 DOSAGE AND ADMINISTRATION

AGGRENOX is not interchangeable with the individual components of aspirin and dipyridamole tablets.

The recommended dose of AGGRENOX is one capsule given orally twice daily, one in the morning and one in the evening. Swallow capsules whole without chewing. AGGRENOX can be administered with or without food.

2.1 Alternative Regimen in Case of Intolerable Headaches

In the event of intolerable headaches during initial treatment, switch to one capsule at bedtime and low-dose aspirin in the morning. Because there are no outcome data with this regimen and headaches become less of a problem as treatment continues, patients should return to the usual regimen as soon as possible, usually within one week.

3 DOSAGE FORMS AND STRENGTHS

25 mg/200 mg capsules with a red cap and an ivory-colored body, containing yellow extended-release pellets incorporating dipyridamole and a round white tablet incorporating immediate-release aspirin. The capsule body is imprinted in red with the Boehringer Ingelheim logo and with "01A".

4 CONTRAINDICATIONS

4.1 Hypersensitivity

AGGRENOX is contraindicated in patients with known hypersensitivity to any of the product components.

4.2 Allergy

Aspirin is contraindicated in patients with known allergy to nonsteroidal anti-inflammatory drug (NSAID) products and in patients with the syndrome of asthma, rhinitis, and nasal polyps. Aspirin may cause severe urticaria, angioedema or bronchospasm.

4.3 Reye Syndrome

Do not use aspirin in children or teenagers with viral infections because of the risk of Reye syndrome.

5 WARNINGS AND PRECAUTIONS

5.1 Risk of Bleeding

AGGRENOX increases the risk of bleeding. Risk factors for bleeding include the use of other drugs that increase the risk of bleeding (e.g., anticoagulants, antiplatelet agents, heparin, anagrelide, fibrinolytic therapy, and chronic use of NSAIDs) [see Drug Interactions (7.1)].

Intracranial Hemorrhage
In European Stroke Prevention Study-2 (ESPS2), the incidence of intracranial hemorrhage was 0.6% in the AGGRENOX group, 0.5% in the extended-release dipyridamole (ER-DP) group, 0.4% in the aspirin (ASA) group and 0.4% in the placebo groups.

Gastrointestinal (GI) Side Effects
GI side effects include stomach pain, heartburn, nausea, vomiting, and gross GI bleeding. Although minor upper GI symptoms, such as dyspepsia, are common and can occur anytime during therapy, physicians should remain alert for signs of ulceration and bleeding, even in the absence of previous GI symptoms. Inform patients about the signs and symptoms of GI side effects and what steps to take if they occur.

In ESPS2, the incidence of gastrointestinal bleeding was 4.1% in the AGGRENOX group, 2.2% in the extended-release dipyridamole group, 3.2% in the aspirin group, and 2.1% in the placebo groups.

Peptic Ulcer Disease
Avoid using aspirin in patients with a history of active peptic ulcer disease, which can cause gastric mucosal irritation and bleeding.

Alcohol Warning
Because AGGRENOX contains aspirin, counsel patients who consume three or more alcoholic drinks every day about the bleeding risks involved with chronic, heavy alcohol use while taking aspirin.

5.2 Renal Failure

Avoid aspirin in patients with severe renal failure (glomerular filtration rate less than 10 mL/minute) [see Use in Specific Populations (8.6) and Clinical Pharmacology (12.3)].

5.3 Hepatic Insufficiency

Elevations of hepatic enzymes and hepatic failure have been reported in association with dipyridamole administration [see Use in Specific Populations (8.6) and Clinical Pharmacology (12.3)].

5.4 Pregnancy

Because AGGRENOX contains aspirin, AGGRENOX can cause fetal harm when administered to a pregnant woman. Maternal aspirin use during later stages of pregnancy may cause low birth weight, increased incidence for intracranial hemorrhage in premature infants, stillbirths and neonatal death. Because of the above and because of the known effects of nonsteroidal anti-inflammatory drugs (NSAIDs) on the fetal cardiovascular system (closure of the ductus arteriosus), avoid AGGRENOX in the third trimester of pregnancy [see Use in Specific Populations (8.1)].

Aspirin has been shown to be teratogenic in rats (spina bifida, exencephaly, microphthalmia and coelosomia) and rabbits (congested fetuses, agenesis of skull and upper jaw, generalized edema with malformation of the head, and diaphanous skin) at oral doses of 330 mg/kg/day and 110 mg/kg/day, respectively. These doses, which also resulted in a high resorption rate in rats (63% of implantations versus 5% in controls), are, on a mg/m^2 basis, about 66 and 44 times, respectively, the dose of aspirin contained in the maximum recommended daily human dose of AGGRENOX. Reproduction studies with dipyridamole have been performed in mice, rabbits and rats at oral doses of up to 125 mg/kg, 40 mg/kg and 1000 mg/kg, respectively (about 1½, 2 and 25 times the maximum recommended daily human oral dose, respectively, on a mg/m^2 basis) and have revealed no evidence of harm to the fetus due to dipyridamole. When 330 mg aspirin/kg/day was combined with 75 mg dipyridamole/kg/day in the rat, the resorption rate approached 100%, indicating potentiation of aspirin-related fetal toxicity. There are no adequate and well-controlled studies of the use of AGGRENOX in pregnant women. If AGGRENOX is used during pregnancy, or if the patient becomes pregnant while taking AGGRENOX, inform the patient of the potential hazard to the fetus.

5.5 Coronary Artery Disease

Dipyridamole has a vasodilatory effect. Chest pain may be precipitated or aggravated in patients with underlying coronary artery disease who are receiving dipyridamole.

For stroke or TIA patients for whom aspirin is indicated to prevent recurrent myocardial infarction (MI) or angina pectoris, the aspirin in this product may not provide adequate treatment for the cardiac indications.

5.6 Hypotension

Dipyridamole produces peripheral vasodilation, which can exacerbate pre-existing hypotension.

5.7 General

AGGRENOX capsules are not interchangeable with the individual components of aspirin and dipyridamole tablets.

6 ADVERSE REACTIONS

The following adverse reactions are discussed elsewhere in the labeling:

- Hypersensitivity [see Contraindications (4.1)]
- Allergy [see Contraindications (4.2)]
- Risk of Bleeding [see Warnings and Precautions (5.1)]

6.1 Clinical Trials Experience

Because clinical trials are conducted under widely varying conditions, adverse reaction rates observed in the clinical trials of a drug cannot be directly compared to rates in the clinical trials of another drug and may not reflect the rates observed in practice.

The efficacy and safety of AGGRENOX was established in the European Stroke Prevention Study-2 (ESPS2). ESPS2 was a double-blind, placebo-controlled study that evaluated 6602 patients over the age of 18 years who had a previous ischemic stroke or transient ischemic attack within ninety days prior to entry. Patients were randomized to either AGGRENOX, aspirin, ER-DP, or placebo [see Clinical Studies (14)]; primary endpoints included stroke (fatal or nonfatal) and death from all causes.

This 24-month, multicenter, double-blind, randomized study (ESPS2) was conducted to compare the efficacy and safety of AGGRENOX with placebo, extended-release dipyridamole alone and aspirin alone. The study was conducted in a total of 6602 male and female patients who had experienced a previous ischemic stroke or transient ischemia of the brain within three months prior to randomization.

Table 1 presents the incidence of adverse events that occurred in 1% or more of patients treated with AGGRENOX where the incidence was also greater than in those patients treated with placebo. There is no clear benefit of the dipyridamole/aspirin combination over aspirin with respect to safety.

Table 1 Incidence of Adverse Events in ESPS2a
 | Individual Treatment Group
 | AGGRENOX |  | ER-DP Alone |  | ASA Alone |  | Placebo
Body System/Preferred Term
 | 1650 |  | 1654 |  | 1649 |  | 1649
Total Number of Patients
Total Number (%) of Patients With at Least One On-Treatment Adverse Event | 1319 | (80%) | 1305 | (79%) | 1323 | (80%) | 1304 | (79%)
Central and Peripheral Nervous System Disorders
Headache | 647 | (39%) | 634 | (38%) | 558 | (34%) | 543 | (33%)
Convulsions | 28 | (2%) | 15 | (1%) | 28 | (2%) | 26 | (2%)
Gastrointestinal System Disorders
Dyspepsia | 303 | (18%) | 288 | (17%) | 299 | (18%) | 275 | (17%)
Abdominal Pain | 289 | (18%) | 255 | (15%) | 262 | (16%) | 239 | (14%)
Nausea | 264 | (16%) | 254 | (15%) | 210 | (13%) | 232 | (14%)
Diarrhea | 210 | (13%) | 257 | (16%) | 112 | (7%) | 161 | (10%)
Vomiting | 138 | (8%) | 129 | (8%) | 101 | (6%) | 118 | (7%)
Hemorrhage Rectum | 26 | (2%) | 22 | (1%) | 16 | (1%) | 13 | (1%)
Melena | 31 | (2%) | 10 | (1%) | 20 | (1%) | 13 | (1%)
Hemorrhoids | 16 | (1%) | 13 | (1%) | 10 | (1%) | 10 | (1%)
GI Hemorrhage | 20 | (1%) | 5 | (0%) | 15 | (1%) | 7 | (0%)
Body as a Whole - General Disorders
Pain | 105 | (6%) | 88 | (5%) | 103 | (6%) | 99 | (6%)
Fatigue | 95 | (6%) | 93 | (6%) | 97 | (6%) | 90 | (5%)
Back Pain | 76 | (5%) | 77 | (5%) | 74 | (4%) | 65 | (4%)
Accidental Injury | 42 | (3%) | 24 | (1%) | 51 | (3%) | 37 | (2%)
Malaise | 27 | (2%) | 23 | (1%) | 26 | (2%) | 22 | (1%)
Asthenia | 29 | (2%) | 19 | (1%) | 17 | (1%) | 18 | (1%)
Syncope | 17 | (1%) | 13 | (1%) | 16 | (1%) | 8 | (0%)
Psychiatric Disorders
Amnesia | 39 | (2%) | 40 | (2%) | 57 | (3%) | 34 | (2%)
Confusion | 18 | (1%) | 9 | (1%) | 22 | (1%) | 15 | (1%)
Anorexia | 19 | (1%) | 17 | (1%) | 10 | (1%) | 15 | (1%)
Somnolence | 20 | (1%) | 13 | (1%) | 18 | (1%) | 9 | (1%)
Musculoskeletal System Disorders
Arthralgia | 91 | (6%) | 75 | (5%) | 91 | (6%) | 76 | (5%)
Arthritis | 34 | (2%) | 25 | (2%) | 17 | (1%) | 19 | (1%)
Arthrosis | 18 | (1%) | 22 | (1%) | 13 | (1%) | 14 | (1%)
Myalgia | 20 | (1%) | 16 | (1%) | 11 | (1%) | 11 | (1%)
Respiratory System Disorders
Coughing | 25 | (2%) | 18 | (1%) | 32 | (2%) | 21 | (1%)
Upper Respiratory Tract Infection | 16 | (1%) | 9 | (1%) | 16 | (1%) | 14 | (1%)
Cardiovascular Disorders, General
Cardiac Failure | 26 | (2%) | 17 | (1%) | 30 | (2%) | 25 | (2%)
Platelet, Bleeding and Clotting Disorders
Hemorrhage NOS | 52 | (3%) | 24 | (1%) | 46 | (3%) | 24 | (1%)
Epistaxis | 39 | (2%) | 16 | (1%) | 45 | (3%) | 25 | (2%)
Purpura | 23 | (1%) | 8 | (0%) | 9 | (1%) | 7 | (0%)
Neoplasm
Neoplasm NOS | 28 | (2%) | 16 | (1%) | 23 | (1%) | 20 | (1%)
Red Blood Cell Disorders
Anemia | 27 | (2%) | 16 | (1%) | 19 | (1%) | 9 | (1%)
aReported by ≥1% of patients during AGGRENOX treatment where the incidence was greater than in those treated with placebo.
Note:              ER-DP = extended-release dipyridamole 200 mg; ASA = aspirin 25 mg. The dosage regimen for all treatment groups is BID. NOS = not otherwise specified.

Discontinuation due to adverse events in ESPS2 was 25% for AGGRENOX, 25% for extended-release dipyridamole, 19% for aspirin, and 21% for placebo (refer to Table 2)

Table 2 Incidence of Adverse Events that Led to the Discontinuation of Treatment: Adverse Events with an Incidence of ≥1% in the AGGRENOX Group
 | Treatment Groups
 | AGGRENOX |  | ER-DP |  | ASA |  | Placebo
Total Number of Patients | 1650 |  | 1654 |  | 1649 |  | 1649
Patients with at least one Adverse Event that led to treatment discontinuation | 417 | (25%) | 419 | (25%) | 318 | (19%) | 352 | (21%)
Headache | 165 | (10%) | 166 | (10%) | 57 | (3%) | 69 | (4%)
Dizziness | 85 | (5%) | 97 | (6%) | 69 | (4%) | 68 | (4%)
Nausea | 91 | (6%) | 95 | (6%) | 51 | (3%) | 53 | (3%)
Abdominal Pain | 74 | (4%) | 64 | (4%) | 56 | (3%) | 52 | (3%)
Dyspepsia | 59 | (4%) | 61 | (4%) | 49 | (3%) | 46 | (3%)
Vomiting | 53 | (3%) | 52 | (3%) | 28 | (2%) | 24 | (1%)
Diarrhea | 35 | (2%) | 41 | (2%) | 9 | (<1%) | 16 | (<1%)
Stroke | 39 | (2%) | 48 | (3%) | 57 | (3%) | 73 | (4%)
Transient Ischemic Attack | 35 | (2%) | 40 | (2%) | 26 | (2%) | 48 | (3%)
Angina Pectoris | 23 | (1%) | 20 | (1%) | 16 | (<1%) | 26 | (2%)
Note:     ER-DP = extended-release dipyridamole 200 mg; ASA = aspirin 25 mg. The dosage regimen for all treatment groups is BID.

Headache was most notable in the first month of treatment.

Other Adverse Events
Adverse reactions that occurred in less than 1% of patients treated with AGGRENOX in the ESPS2 study and that were medically judged to be possibly related to either dipyridamole or aspirin are listed below.

Body as a Whole: Allergic reaction, fever

Cardiovascular: Hypotension

Central Nervous System: Coma, dizziness, paresthesia, cerebral hemorrhage, intracranial hemorrhage, subarachnoid hemorrhage

Gastrointestinal: Gastritis, ulceration and perforation

Hearing and Vestibular Disorders: Tinnitus, and deafness. Patients with high frequency hearing loss may have difficulty perceiving tinnitus. In these patients, tinnitus cannot be used as a clinical indicator of salicylism

Heart Rate and Rhythm Disorders: Tachycardia, palpitation, arrhythmia, supraventricular tachycardia

Liver and Biliary System Disorders: Cholelithiasis, jaundice, hepatic function abnormal

Metabolic and Nutritional Disorders: Hyperglycemia, thirst

Platelet, Bleeding and Clotting Disorders: Hematoma, gingival bleeding

Psychiatric Disorders: Agitation

Reproductive: Uterine hemorrhage

Respiratory: Hyperpnea, asthma, bronchospasm, hemoptysis, pulmonary edema

Special Senses Other Disorders: Taste loss

Skin and Appendages Disorders: Pruritus, urticaria

Urogenital: Renal insufficiency and failure, hematuria

Vascular (Extracardiac) Disorders: Flushing

Laboratory Changes
Over the course of the 24-month study (ESPS2), patients treated with AGGRENOX showed a decline (mean change from baseline) in hemoglobin of 0.25 g/dL, hematocrit of 0.75%, and erythrocyte count of 0.13x10^6/mm^3.

6.2 Post-Marketing Experience

The following is a list of additional adverse reactions that have been reported either in the literature or are from post-marketing spontaneous reports for either dipyridamole or aspirin. Because these reactions are reported voluntarily from a population of uncertain size, it is not always possible to estimate reliably their frequency or establish a causal relationship to drug exposure. Decisions to include these reactions in labeling are typically based on one or more of the following factors: (1) seriousness of the reaction, (2) frequency of reporting, or (3) strength of causal connection to AGGRENOX.

Body as a Whole: Hypothermia, chest pain

Cardiovascular: Angina pectoris

Central Nervous System: Cerebral edema

Fluid and Electrolyte: Hyperkalemia, metabolic acidosis, respiratory alkalosis, hypokalemia

Gastrointestinal: Pancreatitis, Reye syndrome, hematemesis

Hearing and Vestibular Disorders: Hearing loss

Immune System Disorders: Hypersensitivity, acute anaphylaxis, laryngeal edema

Liver and Biliary System Disorders: Hepatitis, hepatic failure

Musculoskeletal: Rhabdomyolysis

Metabolic and Nutritional Disorders: Hypoglycemia, dehydration

Platelet, Bleeding and Clotting Disorders: Prolongation of the prothrombin time, disseminated intravascular coagulation, coagulopathy, thrombocytopenia

Reproductive: Prolonged pregnancy and labor, stillbirths, lower birth weight infants, antepartum and postpartum bleeding

Respiratory: Tachypnea, dyspnea

Skin and Appendages Disorders: Rash, alopecia, angioedema, Stevens-Johnson syndrome, skin hemorrhages such as bruising, ecchymosis, and hematoma

Urogenital: Interstitial nephritis, papillary necrosis, proteinuria

Vascular (Extracardiac) Disorders: Allergic vasculitis

Other Adverse Events: anorexia, aplastic anemia, migraine, pancytopenia, thrombocytosis.

7 DRUG INTERACTIONS

7.1 Drug Interaction Study Information Obtained From Literature

Adenosine
Dipyridamole has been reported to increase the plasma levels and cardiovascular effects of adenosine. Adjustment of adenosine dosage may be necessary.

Angiotensin Converting Enzyme (ACE) Inhibitors
Due to the indirect effect of aspirin on the renin-angiotensin conversion pathway, the hyponatremic and hypotensive effects of ACE inhibitors may be diminished by concomitant administration of aspirin.

Acetazolamide
Concurrent use of aspirin and acetazolamide can lead to high serum concentrations of acetazolamide (and toxicity) due to competition at the renal tubule for secretion.

Anticoagulants and Antiplatelets
Patients taking AGGRENOX in combination with anticoagulants, antiplatelets, or any substance impacting coagulation are at increased risk for bleeding. Aspirin can displace warfarin from protein binding sites, leading to prolongation of both the prothrombin time and the bleeding time. Aspirin can increase the anticoagulant activity of heparin, increasing bleeding risk.

Anagrelide
Patients taking aspirin in combination with anagrelide are at an increased risk of bleeding.

Anticonvulsants
Salicylic acid can displace protein-bound phenytoin and valproic acid, leading to a decrease in the total concentration of phenytoin and an increase in serum valproic acid levels.

Beta Blockers
The hypotensive effects of beta blockers may be diminished by the concomitant administration of aspirin due to inhibition of renal prostaglandins, leading to decreased renal blood flow and salt and fluid retention.

Cholinesterase Inhibitors
Dipyridamole may counteract the anticholinesterase effect of cholinesterase inhibitors, thereby potentially aggravating myasthenia gravis.

Diuretics
The effectiveness of diuretics in patients with underlying renal or cardiovascular disease may be diminished by the concomitant administration of aspirin due to inhibition of renal prostaglandins, leading to decreased renal blood flow and salt and fluid retention.

Methotrexate
Salicylate can inhibit renal clearance of methotrexate, leading to bone marrow toxicity, especially in the elderly or renal impaired.

Nonsteroidal Anti-Inflammatory Drugs (NSAIDs)
The concurrent use of aspirin with other NSAIDs may increase bleeding or lead to decreased renal function.

Oral Hypoglycemics
Moderate doses of aspirin may increase the effectiveness of oral hypoglycemic drugs, leading to hypoglycemia.

Uricosuric Agents (probenecid and sulfinpyrazone)
Salicylates antagonize the uricosuric action of uricosuric agents.

8 USE IN SPECIFIC POPULATIONS

8.1 Pregnancy

Teratogenic Effects, Pregnancy Category D. [see Warnings and Precautions (5.4)].

8.2 Labor and Delivery

Aspirin can result in excessive blood loss at delivery as well as prolonged gestation and prolonged labor. Because of these effects on the mother and because of adverse fetal effects seen with aspirin during the later stages of pregnancy [see Warnings and Precautions (5.4)], avoid AGGRENOX in the third trimester of pregnancy and during labor and delivery.

8.3 Nursing Mothers

Both dipyridamole and aspirin are excreted in human milk. Exercise caution when AGGRENOX capsules are administered to a nursing woman.

8.4 Pediatric Use

Safety and effectiveness of AGGRENOX in pediatric patients have not been studied. Due to the aspirin component, use of this product in the pediatric population is not recommended [see Contraindications (4.3)].

8.5 Geriatric Use

Of the total number of subjects in ESPS2, 61 percent were 65 and over, while 27 percent were 75 and over. No overall differences in safety or effectiveness were observed between these subjects and younger subjects, and other reported clinical experience has not identified differences in responses between the elderly and younger patients, but greater sensitivity of some older individuals cannot be ruled out [see Clinical Pharmacology (12.3)].

8.6 Patients with Severe Hepatic or Severe Renal Dysfunction

AGGRENOX has not been studied in patients with hepatic or renal impairment. Avoid using aspirin containing products, such as AGGRENOX in patients with severe hepatic or severe renal (glomerular filtration rate <10 mL/min) dysfunction [see Warnings and Precautions (5.2, 5.3) and Clinical Pharmacology (12.3)].

10 OVERDOSAGE

Because of the dose ratio of dipyridamole to aspirin, overdosage of AGGRENOX is likely to be dominated by signs and symptoms of dipyridamole overdose. In case of real or suspected overdose, seek medical attention or contact a Poison Control Center immediately. Careful medical management is essential.

Based upon the known hemodynamic effects of dipyridamole, symptoms such as warm feeling, flushes, sweating, restlessness, feeling of weakness and dizziness may occur. A drop in blood pressure and tachycardia might also be observed.

Salicylate toxicity may result from acute ingestion (overdose) or chronic intoxication. Severity of aspirin intoxication is determined by measuring the blood salicylate level. The early signs of salicylic overdose (salicylism), including tinnitus (ringing in the ears), occur at plasma concentrations approaching 200 µg/mL. In severe cases, hyperthermia and hypovolemia are the major immediate threats to life. Plasma concentrations of aspirin above 300 µg/mL are clearly toxic. Severe toxic effects are associated with levels above 400 µg/mL. A single lethal dose of aspirin in adults is not known with certainty but death may be expected at 30 g.

Treatment of overdose consists primarily of supporting vital functions, increasing drug elimination, and correcting acid-base disturbances. Consider gastric emptying and/or lavage as soon as possible after ingestion, even if the patient has vomited spontaneously. After lavage and/or emesis, administration of activated charcoal as a slurry may be beneficial if less than 3 hours have passed since ingestion. Charcoal absorption should not be employed prior to emesis and lavage. Follow acid-base status closely with serial blood gas and serum pH measurements. Maintain fluid and electrolyte balance. Administer replacement fluid intravenously and augment with correction of acidosis. Treatment may require the use of a vasopressor. Infusion of glucose may be required to control hypoglycemia.

Administration of xanthine derivatives (e.g., aminophylline) may reverse the hemodynamic effects of dipyridamole overdose. Plasma electrolytes and pH should be monitored serially to promote alkaline diuresis of salicylate if renal function is normal. In patients with renal insufficiency or in cases of life-threatening intoxication, dialysis is usually required to treat salicylic overdose; however, since dipyridamole is highly protein bound, dialysis is not likely to remove dipyridamole. Exchange transfusion may be indicated in infants and young children.

11 DESCRIPTION

AGGRENOX is a combination antiplatelet agent intended for oral administration. Each hard gelatin capsule contains 200 mg dipyridamole in an extended-release form and 25 mg aspirin, as an immediate-release sugar-coated tablet. In addition, each capsule contains the following inactive ingredients: acacia, aluminum stearate, colloidal silicon dioxide, corn starch, dimethicone, hypromellose, hypromellose phthalate, lactose monohydrate, methacrylic acid copolymer, microcrystalline cellulose, povidone, stearic acid, sucrose, talc, tartaric acid, titanium dioxide and triacetin.

Each capsule shell contains gelatin, red iron oxide and yellow iron oxide, titanium dioxide and water.

Dipyridamole
Dipyridamole is an antiplatelet agent chemically described as 2,2',2'',2'''-[(4,8-Dipiperidinopyrimido[5,4-d]pyrimidine-2,6-diyl)dinitrilo]-tetraethanol. It has the following structural formula:

Dipyridamole is an odorless yellow crystalline substance, having a bitter taste. It is soluble in dilute acids, methanol and chloroform, and is practically insoluble in water.

Aspirin
The antiplatelet agent aspirin (acetylsalicylic acid) is chemically known as benzoic acid, 2- (acetyloxy)-, and has the following structural formula:

Aspirin is an odorless white needle-like crystalline or powdery substance. When exposed to moisture, aspirin hydrolyzes into salicylic and acetic acids, and gives off a vinegary odor. It is highly lipid soluble and slightly soluble in water.

12 CLINICAL PHARMACOLOGY

12.1 Mechanism of Action

The antithrombotic action of AGGRENOX is the result of the additive antiplatelet effects of dipyridamole and aspirin.

Dipyridamole
Dipyridamole inhibits the uptake of adenosine into platelets, endothelial cells and erythrocytes in vitro and in vivo; the inhibition occurs in a dose-dependent manner at therapeutic concentrations (0.5–1.9 µg/mL). This inhibition results in an increase in local concentrations of adenosine which acts on the platelet A2-receptor thereby stimulating platelet adenylate cyclase and increasing platelet cyclic-3',5'-adenosine monophosphate (cAMP) levels. Via this mechanism, platelet aggregation is inhibited in response to various stimuli such as platelet activating factor (PAF), collagen and adenosine diphosphate (ADP).

Dipyridamole inhibits phosphodiesterase (PDE) in various tissues. While the inhibition of cAMP-PDE is weak, therapeutic levels of dipyridamole inhibit cyclic-3',5'-guanosine monophosphate-PDE (cGMP-PDE), thereby augmenting the increase in cGMP produced by EDRF (endothelium-derived relaxing factor, now identified as nitric oxide).

Aspirin
Aspirin inhibits platelet aggregation by irreversible inhibition of platelet cyclooxygenase and thus inhibits the generation of thromboxane A2, a powerful inducer of platelet aggregation and vasoconstriction.

12.2 Pharmacodynamics

The effect of either agent on the other's inhibition of platelet reactivity has not been evaluated.

12.3 Pharmacokinetics

There are no significant interactions between aspirin and dipyridamole. The kinetics of the components are unchanged by their co-administration as AGGRENOX.

Dipyridamole
Absorption
Peak plasma levels of dipyridamole are achieved 2 hours (range 1–6 hours) after administration of a daily dose of 400 mg AGGRENOX (given as 200 mg BID). The peak plasma concentration at steady-state is 1.98 µg/mL (1.01–3.99 µg/mL) and the steady-state trough concentration is 0.53 µg/mL (0.18–1.01 µg/mL).

Effect of Food
When AGGRENOX capsules were taken with a high fat meal, dipyridamole peak plasma levels (Cmax) and total absorption (AUC) were decreased at steady-state by 20-30% compared to fasting. Due to the similar degree of inhibition of adenosine uptake at these plasma concentrations, this food effect is not considered clinically relevant.

Distribution
Dipyridamole is highly lipophilic (log P=3.71, pH=7); however, it has been shown that the drug does not cross the blood-brain barrier to any significant extent in animals. The steady-state volume of distribution of dipyridamole is about 92 L. Approximately 99% of dipyridamole is bound to plasma proteins, predominantly to alpha 1-acid glycoprotein and albumin.

Metabolism and Elimination
Dipyridamole is metabolized in the liver, primarily by conjugation with glucuronic acid, of which monoglucuronide which has low pharmacodynamic activity is the primary metabolite. In plasma, about 80% of the total amount is present as parent compound and 20% as monoglucuronide. Most of the glucuronide metabolite (about 95%) is excreted via bile into the feces, with some evidence of enterohepatic circulation. Renal excretion of parent compound is negligible and urinary excretion of the glucuronide metabolite is low (about 5%). With intravenous (i.v.) treatment of dipyridamole, a triphasic profile is obtained: a rapid alpha phase, with a half-life of about 3.4 minutes, a beta phase, with a half-life of about 39 minutes, (which, together with the alpha phase accounts for about 70% of the total area under the curve, AUC) and a prolonged elimination phase λz with a half-life of about 15.5 hours. Due to the extended absorption phase of the dipyridamole component, only the terminal phase is apparent from oral treatment with AGGRENOX which, in Trial 9.123 was 13.6 hours.

Special Populations

Geriatric Patients: In ESPS2 [see Clinical Studies (14)], plasma concentrations (determined as AUC) of dipyridamole in healthy elderly subjects (>65 years) were about 40% higher than in subjects younger than 55 years receiving treatment with AGGRENOX.

Hepatic Dysfunction: No study has been conducted with AGGRENOX in patients with hepatic dysfunction.

In a study conducted with an intravenous formulation of dipyridamole, patients with mild to severe hepatic insufficiency showed no change in plasma concentrations of dipyridamole but showed an increase in the pharmacologically inactive monoglucuronide metabolite. Dipyridamole can be dosed without restriction as long as there is no evidence of hepatic failure.

Renal Dysfunction: No study has been conducted with AGGRENOX in patients with renal dysfunction.

In ESPS2 patients [see Clinical Studies (14)], with creatinine clearances ranging from about 15 mL/min to >100 mL/min, no changes were observed in the pharmacokinetics of dipyridamole or its glucuronide metabolite if data were corrected for differences in age.

Aspirin
Absorption
Peak plasma levels of aspirin are achieved 0.63 hours (0.5–1 hour) after administration of a 50 mg aspirin daily dose from AGGRENOX (given as 25 mg BID). The peak plasma concentration at steady-state is 319 ng/mL (175–463 ng/mL). Aspirin undergoes moderate hydrolysis to salicylic acid in the liver and the gastrointestinal wall, with 50%–75% of an administered dose reaching the systemic circulation as intact aspirin.

Effect of Food
When AGGRENOX capsules were taken with a high fat meal, there was no difference for aspirin in AUC at steady-state, and the approximately 50% decrease in Cmax was not considered clinically relevant based on a similar degree of cyclooxygenase inhibition comparing the fed and fasted state.

Distribution
Aspirin is poorly bound to plasma proteins and its apparent volume of distribution is low (10 L). Its metabolite, salicylic acid, is highly bound to plasma proteins, but its binding is concentration-dependent (nonlinear). At low concentrations (<100 µg/mL), approximately 90% of salicylic acid is bound to albumin. Salicylic acid is widely distributed to all tissues and fluids in the body, including the central nervous system, breast milk, and fetal tissues. Early signs of salicylate overdose (salicylism), including tinnitus (ringing in the ears), occur at plasma concentrations approximating 200 µg/mL [see Adverse Reactions (6) and Overdosage (10)].

Metabolism and Elimination
Aspirin is rapidly hydrolyzed in plasma to salicylic acid, with a half-life of 20 minutes. Plasma levels of aspirin are essentially undetectable 2–2.5 hours after dosing and peak salicylic acid concentrations occur 1 hour (range: 0.5–2 hours) after administration of aspirin. Salicylic acid is primarily conjugated in the liver to form salicyluric acid, a phenolic glucuronide, an acyl glucuronide, and a number of minor metabolites. Salicylate metabolism is saturable and total body clearance decreases at higher serum concentrations due to the limited ability of the liver to form both salicyluric acid and phenolic glucuronide. Following toxic doses (10–20 g), the plasma half-life may be increased to over 20 hours.

The elimination of acetylsalicylic acid follows first-order kinetics with AGGRENOX and has a half-life of 0.33 hours. The half-life of salicylic acid is 1.71 hours. Both values correspond well with data from the literature at lower doses which state a resultant half-life of approximately 2–3 hours. At higher doses, the elimination of salicylic acid follows zero-order kinetics (i.e., the rate of elimination is constant in relation to plasma concentration), with an apparent half-life of 6 hours or higher. Renal excretion of unchanged drug depends upon urinary pH. As urinary pH rises above 6.5, the renal clearance of free salicylate increases from <5% to >80%. Alkalinization of the urine is a key concept in the management of salicylate overdose [see Overdosage (10)]. Following therapeutic doses, about 10% is excreted as salicylic acid and 75% as salicyluric acid, as the phenolic and acyl glucuronides, in urine.

Special Populations
Hepatic Dysfunction: Avoid aspirin in patients with severe hepatic insufficiency.

Renal Dysfunction: Avoid aspirin in patients with severe renal failure (glomerular filtration rate less than 10 mL/min).

AGGRENOX
Drug Interaction
A dedicated drug interaction study was conducted in 60 healthy volunteers to evaluate the effects of omeprazole 80 mg administered once daily on the pharmacokinetics (PK) of dipyridamole and the pharmacodynamics (PD) of acetylsalicylic acid when co-administered with AGGRENOX twice daily. Dipyridamole exposure (Cmax and AUC) at steady-state were similar with or without omeprazole co-administration. The pharmacokinetics of acetylsalicylic acid was not characterized. However, the antiplatelet activity as measured by arachidonic acid induced platelet aggregation was similar between the treatment arms at steady-state.

13 NONCLINICAL TOXICOLOGY

13.1 Carcinogenesis, Mutagenesis, Impairment of Fertility

In studies in which dipyridamole was administered in the feed to mice (up to 111 weeks in males and females) and rats (up to 128 weeks in males and up to 142 weeks in females), there was no evidence of drug-related carcinogenesis. The highest dose administered in these studies (75 mg/kg/day) was, on a mg/m^2 basis, about equivalent to the maximum recommended daily human oral dose (MRHD) in mice and about twice the MRHD in rats.

Combinations of dipyridamole and aspirin (1:5 ratio) tested negative in the Ames test, in vivo chromosome aberration tests (in mice and hamsters), oral micronucleus tests (in mice and hamsters) and oral dominant lethal test (in mice). Aspirin, alone, induced chromosome aberrations in cultured human fibroblasts. Mutagenicity tests of dipyridamole alone with bacterial and mammalian cell systems were negative.

Combinations of dipyridamole and aspirin have not been evaluated for effects on fertility and reproductive performance. There was no evidence of impaired fertility when dipyridamole was administered to male and female rats at oral doses up to 500 mg/kg/day (about 12 times the MRHD on a mg/m^2 basis). A significant reduction in number of corpora lutea with consequent reduction in implantations and live fetuses was, however, observed at 1250 mg/kg (more than 30 times the MRHD on a mg/m^2 basis). Aspirin inhibits ovulation in rats.

14 CLINICAL STUDIES

ESPS2 (European Stroke Prevention Study-2) was a double-blind, placebo-controlled, 24-month study in which 6602 patients over the age of 18 years had an ischemic stroke (76%) or transient ischemic attack (TIA, 24%) within three months prior to entry. Patients were enrolled in 13 European countries between February 1989 and May 1995 and were randomized to one of four treatment groups: AGGRENOX (aspirin/extended-release dipyridamole) 25 mg/200 mg; extended-release dipyridamole (ER-DP) 200 mg alone; aspirin (ASA) 25 mg alone; or placebo. The mean age in this population was 66.7 years with 58% of them being males. Patients received one capsule twice daily (morning and evening). Efficacy assessments included analyses of stroke (fatal or nonfatal) and death (from all causes) as confirmed by a blinded morbidity and mortality assessment group. There were no differences with regard to efficacy based on age or gender; patients who were older had a trend towards more events.

Stroke Endpoint
AGGRENOX reduced the risk of stroke by 22.1% compared to aspirin 50 mg/day alone (p = 0.008) and reduced the risk of stroke by 24.4% compared to extended-release dipyridamole 400 mg/day alone (p = 0.002) (Table 3). AGGRENOX reduced the risk of stroke by 36.8% compared to placebo (p <0.001).

Table 3 Summary of First Stroke (Fatal or Nonfatal): ESPS2: Intent-to-Treat Population
 | Total Number of Patients n | Number of Patients With Stroke Within 2 Years n (%) | Kaplan-Meier Estimate of Survival at 2 Years (95% C.I.) | Gehan-Wilcoxon Test P-value | Risk Reduction at 2 Years | Odds Ratio (95% C.I.)
Individual Treatment
Group
AGGRENOX | 1650 | 157 (9.5%) | 89.9% (88.4%, 91.4%) | - | - | -
ER-DP | 1654 | 211 (12.8%) | 86.7% (85.0%, 88.4%) | - | - | -
ASA | 1649 | 206 (12.5%) | 87.1% (85.4%, 88.7%) | - | - | -
Placebo | 1649 | 250 (15.2%) | 84.1% (82.2%, 85.9%) | - | - | -
Pairwise Treatment Group Comparisons
AGGRENOX        vs. ER-DP | - | - | - | 0.002b | 24.4% | 0.72 (0.58, 0.90)
AGGRENOX        vs. ASA | - | - | - | 0.008b | 22.1% | 0.74 (0.59, 0.92)
AGGRENOX        vs. Placebo | - | - | - | <0.001b | 36.8% | 0.59 (0.48, 0.73)
ER-DP vs. Placebo | - | - | - | 0.036a | 16.5% | 0.82 (0.67, 1.00)
ASA vs. Placebo | - | - | - | 0.009b | 18.9% | 0.80 (0.66, 0.97)
a0.010 <p‑value ≤0.050; bp‑value ≤0.010.
Note: ER-DP = extended-release dipyridamole 200 mg; ASA = aspirin 25 mg. The dosage regimen for all treatment groups is BID.

ESPS2: Cumulative Stroke Rate (Fatal or Nonfatal)
Over 24 months of Follow-UP

Combined Stroke or Death Endpoint
In ESPS2, AGGRENOX reduced the risk of stroke or death by 12.1% compared to aspirin alone and by 10.3% compared to extended-release dipyridamole alone. These results were not statistically significant. AGGRENOX reduced the risk of stroke or death by 24.2% compared to placebo.

Death Endpoint
The incidence rate of all-cause mortality was 11.3% for AGGRENOX, 11.0% for aspirin alone, 11.4% for extended-release dipyridamole alone and 12.3% for placebo alone. The differences between the AGGRENOX, aspirin alone and extended-release dipyridamole alone treatment groups were not statistically significant. These incidence rates for AGGRENOX and aspirin alone are consistent with previous aspirin studies in stroke and TIA patients.

16 HOW SUPPLIED/STORAGE AND HANDLING

AGGRENOX capsules are available as a hard gelatin capsule, with a red cap and an ivory-colored body, containing yellow extended-release pellets incorporating dipyridamole and a round white tablet incorporating immediate-release aspirin. The capsule body is imprinted in red with the Boehringer Ingelheim logo and with "01A".

AGGRENOX capsules are supplied in unit-of-use bottles of 60 capsules (NDC 0597-0001-60).

Store at 25°C (77°F); excursions permitted to 15°-30°C (59°-86°F) [see USP Controlled Room Temperature]. Protect from excessive moisture.

17 PATIENT COUNSELING INFORMATION

Advise the patient to read the FDA-approved patient labeling (Patient Information).

- Risk of Bleeding
  Inform patients that as with other antiplatelet agents, there is a general risk of bleeding including intracranial and gastrointestinal bleeding. Inform patients about the signs and symptoms of bleeding, including occult bleeding. Tell patients to notify their physician if they are prescribed any drug which may increase risk of bleeding.
  Counsel patients who consume three or more alcoholic drinks daily about the bleeding risks involved with chronic, heavy alcohol use while taking aspirin.
- Pregnancy
  Inform patients that aspirin is known to be harmful to fetuses and ask the patient to notify them if they are or become pregnant.
- Headaches
  Some patients may experience headaches upon treatment initiation; these are usually transient. In case of intolerable headaches, tell patients to contact their physician.
- Dosage and Administration
  Tell patients that AGGRENOX capsules should be swallowed whole, and not chewed or crushed. If you miss a dose, continue with your next dose on your regular schedule. Do not take a double dose.
- Storage
  Inform patients to protect AGGRENOX from moisture.

Distributed by:
Boehringer Ingelheim Pharmaceuticals, Inc.
Ridgefield, CT 06877 USA

Licensed from:
Boehringer Ingelheim International GmbH

Copyright © 2015 Boehringer Ingelheim International GmbH
ALL RIGHTS RESERVED

OT1000MK132015
302420-02

Patient Information

Aggrenox® (AG-reh-nox)
(aspirin/extended-release dipyridamole)
Capsules

Read this Patient Information before you start taking AGGRENOX and each time you get a refill. There may be new information. This information does not take the place of talking to your healthcare provider about your medical condition or your treatment.

What is AGGRENOX?

AGGRENOX is a prescription medicine that contains aspirin and a medicine that is slowly released in your body, called dipyridamole. AGGRENOX is used to lower the risk of stroke in people who have had a "mini-stroke" (transient ischemic attack or TIA) or stroke due to a blood clot.

It is not known if AGGRENOX is safe and effective in children. See "Who should not take AGGRENOX?"

Who should not take AGGRENOX?

Do not take AGGRENOX if you:

- are allergic to any of the ingredients in AGGRENOX. See the end of this leaflet for a list of ingredients in AGGRENOX.
- are allergic to non-steroidal anti-inflammatory drugs (NSAIDs)
- have asthma in combination with runny nose and nasal polyps

Do not give AGGRENOX to a child or teenager with a viral illness. Reye syndrome, a life-threatening condition, can happen when aspirin (an ingredient in AGGRENOX) is used in children and teenagers who have certain viral illnesses.

What should I tell my doctor before using AGGRENOX?

Before taking AGGRENOX, tell your healthcare provider if you:

- have stomach ulcers
- have a history of bleeding problems
- have heart problems
- have kidney or liver problems
- have low blood pressure
- have myasthenia gravis
- have any other medical conditions
- are pregnant or plan to become pregnant. AGGRENOX can harm your unborn baby, especially if you take it in the last (third) trimester of pregnancy. You should not take AGGRENOX during pregnancy without first talking to your healthcare provider. Tell your healthcare provider right away if you become pregnant while taking AGGRENOX.
- are breast-feeding or plan to breast-feed. AGGRENOX can pass into your milk and may harm your baby. Talk to your healthcare provider about the best way to feed your baby if you take AGGRENOX.

Tell your doctor about all the medicines you take, including prescription and non-prescription medicines, vitamins and herbal supplements. AGGRENOX and other medicines may affect each other causing side effects. AGGRENOX may affect the way other medicines work, and other medicines may affect how AGGRENOX works.

Especially tell your healthcare provider if you take:

- a medicine for high blood pressure, irregular heart beat, or heart failure
- acetazolamide [Diamox®]
- any blood thinner medicines
- warfarin sodium [Coumadin®, Jantoven®]
- a heparin medicine
- anagrelide [Agrylin®]
- a seizure medicine
- a medicine for Alzheimer’s disease
- a water pill
- methotrexate sodium [Trexall®]
- aspirin or a non-steroidal anti-inflammatory drug (NSAIDs). You should not take NSAIDs during treatment with AGGRENOX. Using these medicines with AGGRENOX can increase your risk of bleeding.
- a medicine for diabetes
- probenecid [Probalan®, Col-Probenecid®]

Ask your healthcare provider or pharmacist if you are not sure if your medicine is one that is listed above.

Know the medicines you take. Keep a list of them and show your healthcare provider and pharmacist when you get a new medicine.

How should I take AGGRENOX?

- Take AGGRENOX exactly as prescribed. Your healthcare provider will tell you how many AGGRENOX to take and when to take them.
- Headaches are not uncommon when you first start taking AGGRENOX, but often lessen as treatment continues. Tell your healthcare provider if you have a severe headache. Your healthcare provider may change the instructions for taking AGGRENOX.
- Swallow AGGRENOX whole. Do not crush or chew the capsules.
- You can take AGGRENOX with or without food.
- If you miss a dose, take your next dose at the usual time. Do not take two doses at one time.
- If you take more AGGRENOX (overdose) than prescribed, call your healthcare provider or Poison Control Center, or get emergency help right away.

Symptoms of an overdose of AGGRENOX include:

- a warm feeling or flushing
- sweating
- restlessness
- weakness or dizziness
- a fast heart rate
- ringing in the ears

What should I avoid while using AGGRENOX?

- heavy alcohol use. People who drink three or more alcoholic drinks every day have a higher risk of bleeding during treatment with AGGRENOX, because it contains aspirin.

What are the possible side effects of AGGRENOX?

AGGRENOX may cause serious side effects, including:

- increased risk of bleeding. You may bleed more easily during AGGRENOX treatment, and it may take longer than usual for bleeding to stop. This can include:
  - bleeding into your brain (intracranial hemorrhage). This can be a medical emergency. Get medical help right away if you have any of these symptoms while taking AGGRENOX:
    - severe headache with drowsiness
    - confusion or memory change
    - pass out (become unconscious)
  - bleeding in your stomach or intestine.
    - stomach pain
    - heartburn or nausea
    - vomiting blood or vomit looks like "coffee grounds"
    - red or bloody stools
    - black stools that look like tar
- new or worsening chest pain in some people with heart disease. Tell your healthcare provider if you have new chest pain or have any change in your chest pain during treatment with AGGRENOX.
- liver problems, including increased liver function tests and liver failure. Tell your healthcare provider if you have any of these symptoms of a liver problem while taking AGGRENOX:
  - loss of appetite
  - pale colored stool
  - stomach area (abdomen) pain
  - yellowing of your skin or whites of your eyes
  - dark urine
  - itching

Call your healthcare provider right away if you have any of the symptoms listed above.

The most common side effects of AGGRENOX include:

- headache
- upset stomach
- diarrhea

These are not all the possible side effects of AGGRENOX. Tell your healthcare provider or pharmacist if you have any side effect that bothers you or that does not go away.

Call your healthcare provider for medical advice about side effects. You may report side effects to FDA at 1-800-FDA-1088.

How should I store AGGRENOX?

- Store AGGRENOX at 59°F to 86°F (15°C to 30°C).
- Keep AGGRENOX capsules dry.
- Safely throw away medicine that is out of date or no longer needed.

Keep AGGRENOX and all medicines out of the reach of children.

General information about AGGRENOX

Medicines are sometimes prescribed for purposes other than those listed in the Patient Information. Do not use AGGRENOX for a condition for which it was not prescribed. Do not give AGGRENOX to other people, even if they have the same symptoms that you have. It may harm them.

This Patient Information summarizes the most important information about AGGRENOX. If you would like more information, talk with your healthcare provider. You can ask your pharmacist or healthcare provider for information about AGGRENOX that is written for health professionals.

For more information, go to www.Aggrenox.com, scan the code below or call Boehringer Ingelheim Pharmaceuticals, Inc. at 1-800-542-6257 or (TTY) 1-800-459-9906.

What are the ingredients in AGGRENOX?

Active Ingredients: dipyridamole in an extended-release form and aspirin
Inactive Ingredients: acacia, aluminum stearate, colloidal silicon dioxide, corn starch, dimethicone, hypromellose, hypromellose phthalate, lactose monohydrate, methacrylic acid copolymer, microcrystalline cellulose, povidone, stearic acid, sucrose, talc, tartaric acid, titanium dioxide and triacetin. Each capsule shell contains gelatin, red iron oxide and yellow iron oxide, titanium dioxide, and water.

Distributed by:
Boehringer Ingelheim Pharmaceuticals, Inc.
Ridgefield, CT 06877 USA

Licensed from:
Boehringer Ingelheim International GmbH

Copyright © 2015 Boehringer Ingelheim International GmbH
ALL RIGHTS RESERVED

Revised: November 2015

OT1000MK132015
302420-02